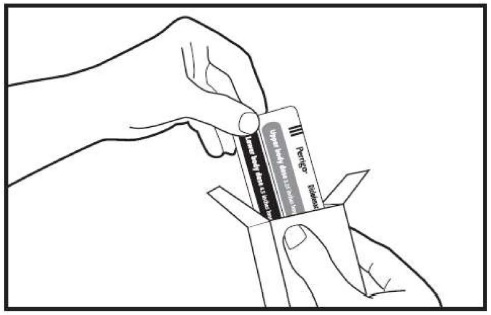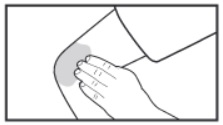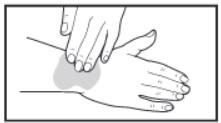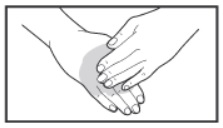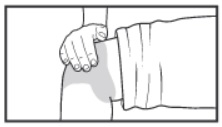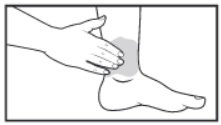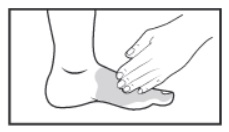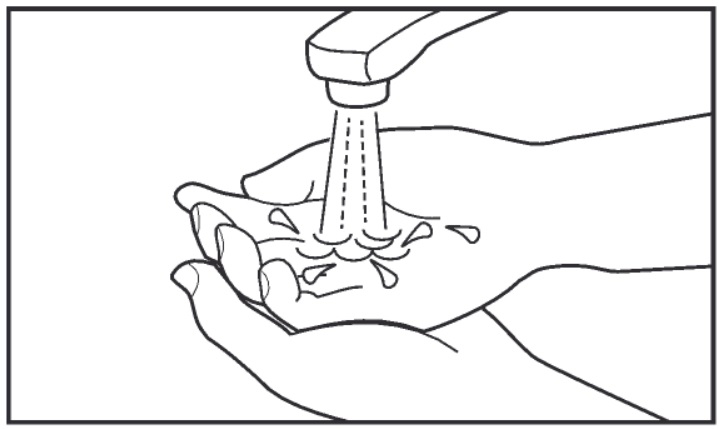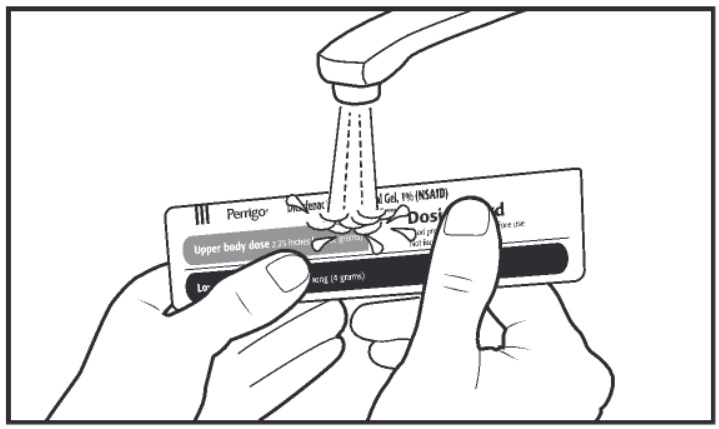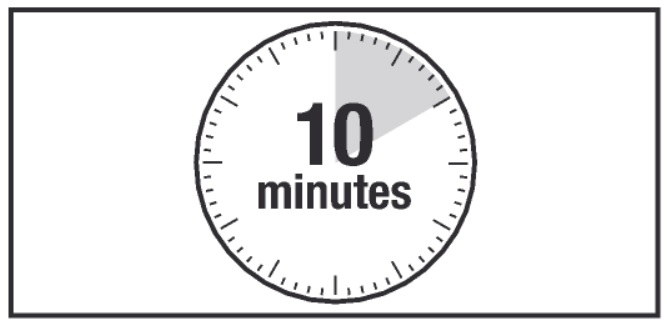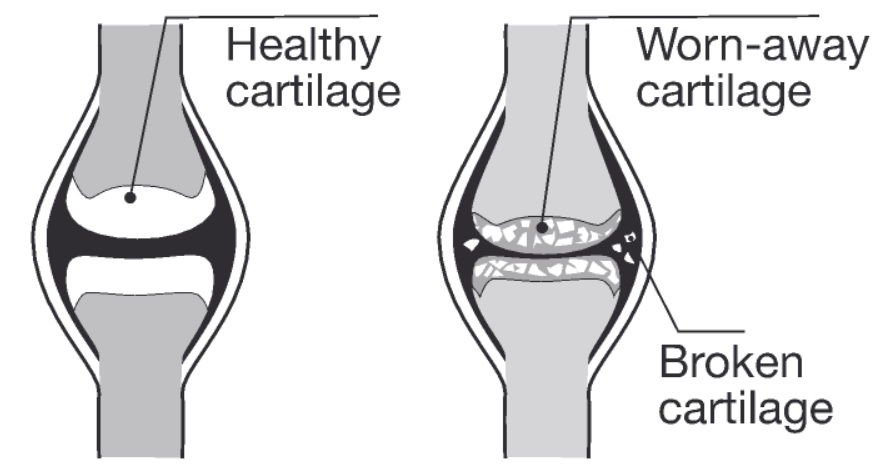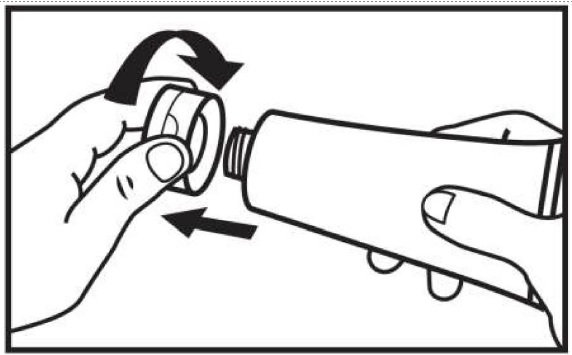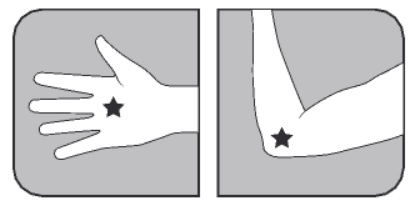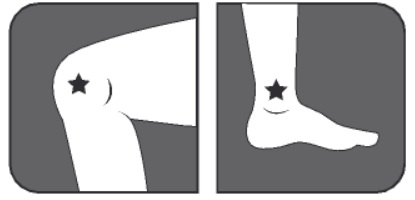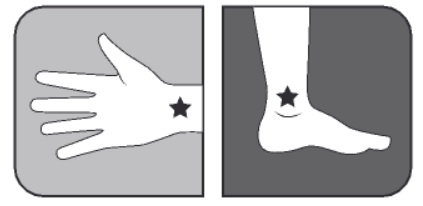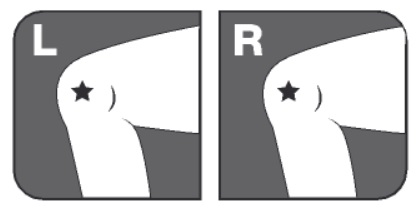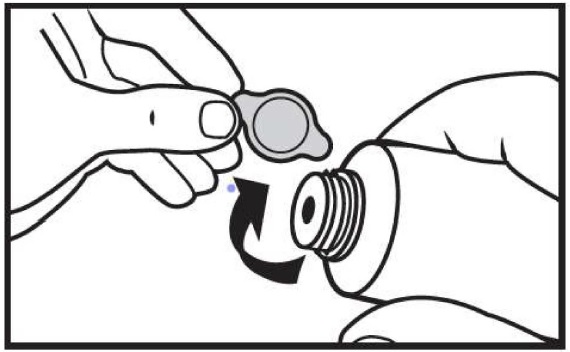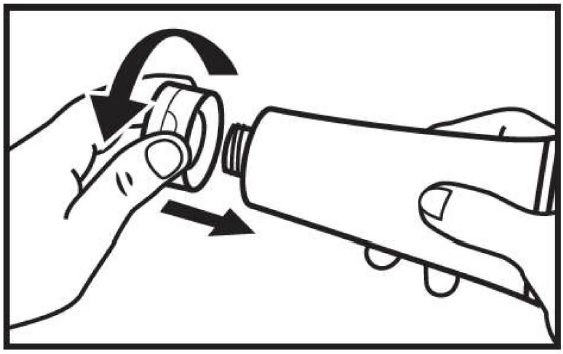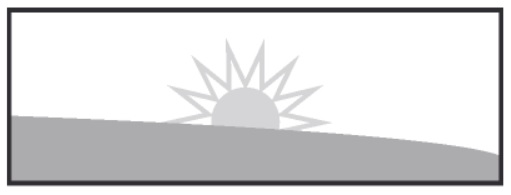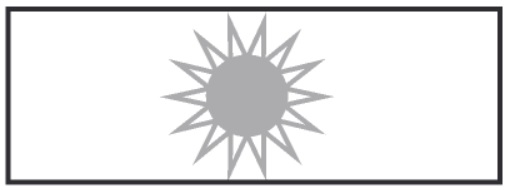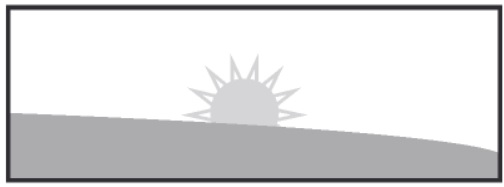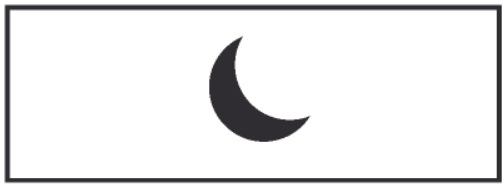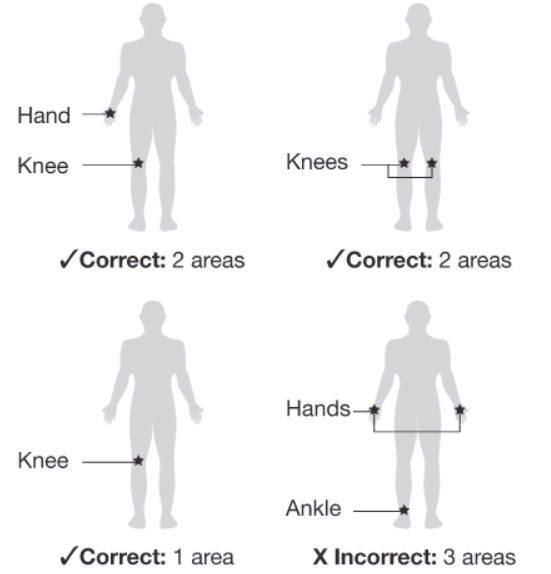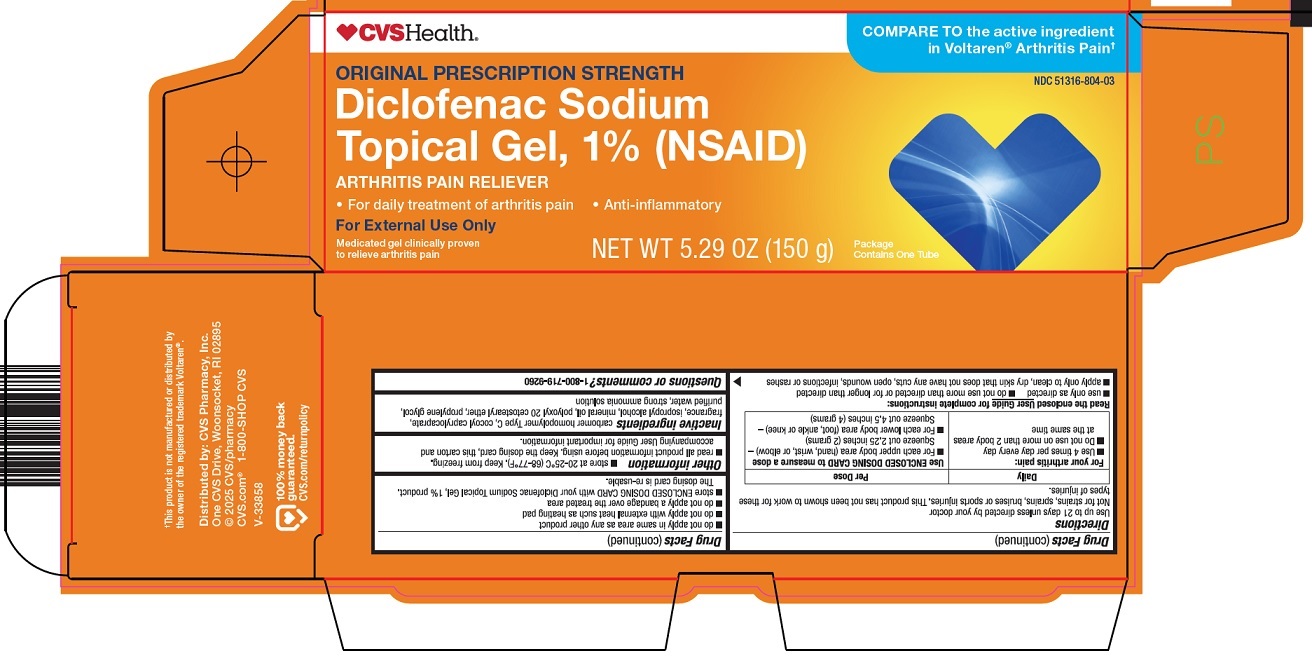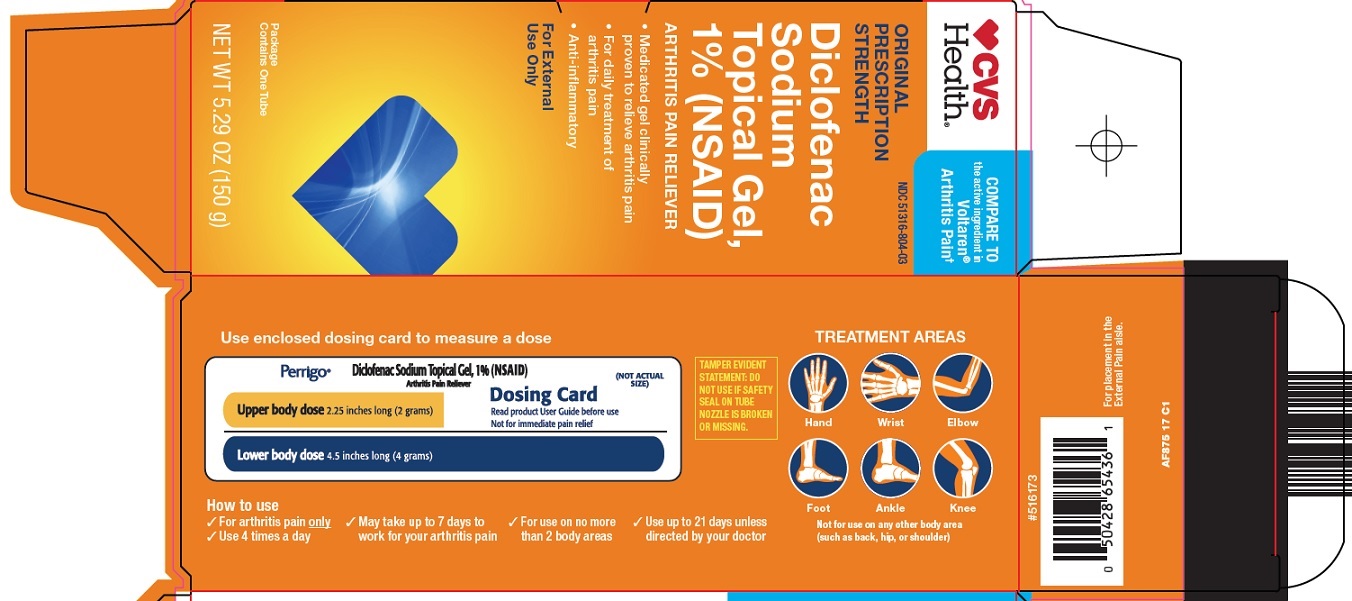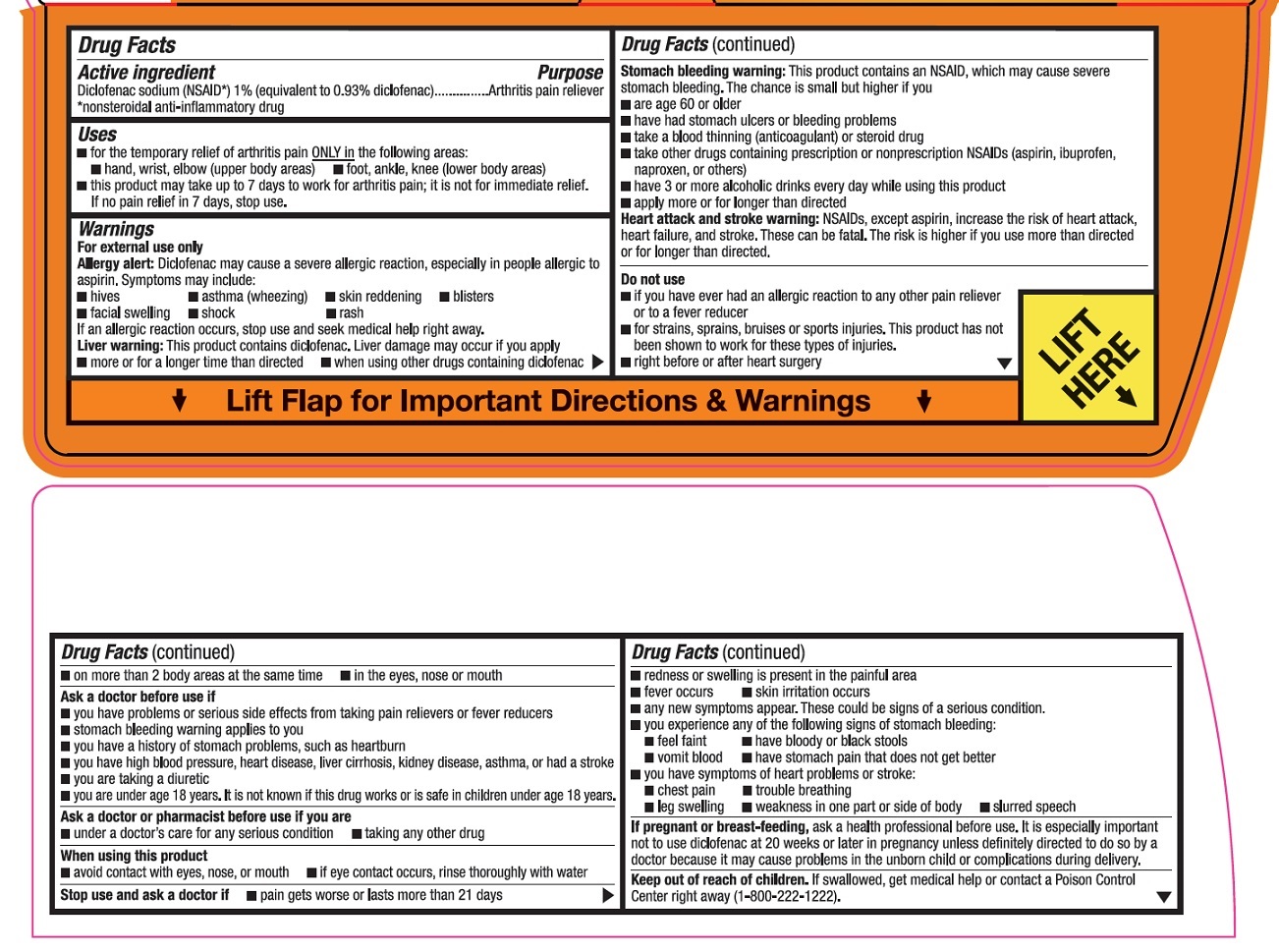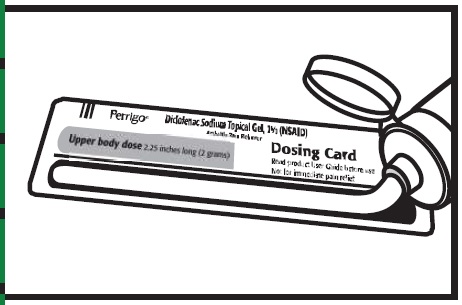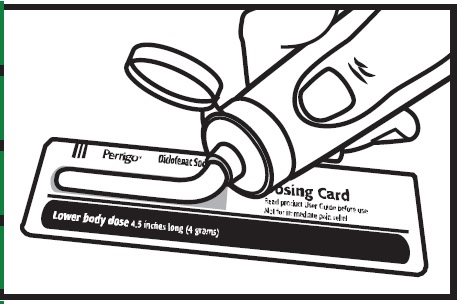 DRUG LABEL: DICLOFENAC SODIUM TOPICAL
NDC: 51316-804 | Form: GEL
Manufacturer: CVS WOONSOCKET PRESCRIPTION CENTER, INCORPORATED
Category: otc | Type: HUMAN OTC DRUG LABEL
Date: 20260115

ACTIVE INGREDIENTS: DICLOFENAC SODIUM 10 mg/1 g
INACTIVE INGREDIENTS: CARBOMER HOMOPOLYMER TYPE C (ALLYL PENTAERYTHRITOL CROSSLINKED); COCOYL CAPRYLOCAPRATE; ISOPROPYL ALCOHOL; MINERAL OIL; POLYOXYL 20 CETOSTEARYL ETHER; PROPYLENE GLYCOL; WATER; AMMONIA

CVS Pharmacy, Inc. Diclofenac Sodium Topical Gel, 1% (NSAID) Drug Facts

Active ingredient

Diclofenac sodium (NSAID*) 1% (equivalent to 0.93% diclofenac)

*nonsteroidal anti-inflammatory drug

Purpose

Arthritis pain reliever

Uses

- for the temporary relief of arthritis pain ONLY in the following areas:
  - hand, wrist, elbow (upper body areas)
  - foot, ankle, knee (lower body areas)
- this product may take up to 7 days to work for arthritis pain; it is not for immediate relief. If no pain relief in 7 days, stop use.

Warnings

For external use only

Allergy alert: Diclofenac may cause a severe allergic reaction, especially in people allergic to aspirin.

Symptoms may include:

- hives
- asthma (wheezing)
- skin reddening
- blisters
- facial swelling
- shock
- rash

If an allergic reaction occurs, stop use and seek medical help right away.

Liver warning: This product contains diclofenac. Liver damage may occur if you apply

- more or for a longer time than directed
- when using other drugs containing diclofenac

Stomach bleeding warning: This product contains an NSAID, which may cause severe stomach bleeding. The chance is small but higher if you

- are age 60 or older
- have had stomach ulcers or bleeding problems
- take a blood thinning (anticoagulant) or steroid drug
- take other drugs containing prescription or nonprescription NSAIDs (aspirin, ibuprofen, naproxen, or others)
- have 3 or more alcoholic drinks every day while using this product
- apply more or for longer than directed

Heart attack and stroke warning: NSAIDs, except aspirin, increase the risk of heart attack, heart failure, and stroke. These can be fatal. The risk is higher is you use more than directed or for longer than directed.

Do not use

- if you have ever had an allergic reaction to any other pain reliever or to a fever reducer
- for strains, sprains, bruises or sports injuries. This product has not been shown to work for these types of injuries.
- right before or after heart surgery
- on more than 2 body areas at the same time
- in the eyes, nose or mouth

Ask a doctor before use if

- you have problems or serious side effects from taking pain relievers or fever reducers
- stomach bleeding warning applies to you
- you have a history of stomach problems, such as heartburn
- you have high blood pressure, heart disease, liver cirrhosis, kidney disease, asthma, or had a stroke
- you are taking a diuretic
- you are under age 18 years. It is not known if this drug works or is safe in children under age 18 years.

Ask a doctor or pharmacist before use if you are

- under a doctor’s care for any serious condition
- taking any other drug

When using this product

- avoid contact with eyes, nose, or mouth
- if eye contact occurs, rinse thoroughly with water

Stop use and ask a doctor if

- pain gets worse or lasts more than 21 days
- redness or swelling is present in the painful area
- fever occurs
- skin irritation occurs
- any new symptoms appear. These could be signs of a serious condition.
- you experience any of the following signs of stomach bleeding:
  - feel faint
  - have bloody or black stools
  - vomit blood
  - have stomach pain that does not get better
- you have symptoms of heart problems or stroke:
  - chest pain
  - trouble breathing
  - leg swelling
  - weakness in one part or side of body
  - slurred speech

If pregnant or breast feeding,

ask a health professional before use. It is especially important not to use diclofenac at 20 weeks or later in pregnancy unless definitely directed to do so by a doctor because it may cause problems in the unborn child or complications during delivery.

Keep out of reach of children.

If swallowed, get medical help or contact a Poison Control Center right away (1-800-222-1222).

Directions

Use up to 21 days unless directed by your doctor

Not for strains, sprains, bruises or sports injuries. This product has not been shown to work for these types of injuries.

Daily | Per Dose
For your arthritis pain:; - Use 4 times per day every day - Do not use on more than 2 body areas at the same time | Use ENCLOSED DOSING CARD to measure a dose; - For each upper body area (hand, wrist, or elbow) – Squeeze out 2.25 inches (2 grams) - For each lower body area (foot, ankle or knee) – Squeeze out 4.5 inches (4 grams)

Read the enclosed User Guide for complete instructions:

- use only as directed
- do not use more than directed or for longer than directed
- apply only to clean, dry skin that does not have any cuts, open wounds, infections or rashes
- do not apply in the same area as any other product
- do not apply with external heat such as heating pad
- do not apply a bandage over the treated area
- store ENCLOSED DOSING CARD with your Diclofenac Sodium Topical Gel, 1% product. The dosing card is re-usable.

Other information

- store at 20-25°C (68-77°F). Keep from freezing.
- read all product information before using. Keep the dosing card, this carton and accompanying User Guide for important information.

Inactive ingredients

carbomer homopolymer Type C, cocoyl caprylocaprate, fragrance, isopropyl alcohol, mineral oil, polyoxyl 20 cetostearyl ether, propylene glycol, purified water, strong ammonia solution

Questions or comments?

1-800-719-9260

Consumer Information

Diclofenac Sodium Topical Gel, 1% (NSAID)

Arthritis Pain Reliever

User Guide

How to use Diclofenac Sodium Topical Gel, 1% with answers to frequently asked questions

Quick Start

How to get started right away with Diclofenac Sodium Topical Gel, 1%

Understanding Diclofenac Sodium Topical Gel, 1%

Diclofenac Sodium Topical Gel, 1% (NSAID) - arthritis pain reliever is an arthritis pain relief medication that you apply to your skin. It is intended to be used 4 times a day every day for up to 21 days.

Before You Use Diclofenac Sodium Topical Gel, 1%

Read the Drug Facts Label, which appears on the carton.

Remove the dosing card from the inside of the carton. You should always use the dosing card to measure out the correct dose of Diclofenac Sodium Topical Gel, 1%.

The first time you use a tube of Diclofenac Sodium Topical Gel, 1%:

1. Take the flip top cap off the tube.

2. Open the safety seal by lifting and pulling the foil tab to remove foil safety seal from tube. Do not open the safety seal with scissors or other sharp objects.

3. After use, put the flip top cap back on the end of the tube.

Using Diclofenac Sodium Topical Gel, 1%

How often to use Diclofenac Sodium Topical Gel, 1%

Use 4 times a day for best results.

For example:

Start of the day

Middle of the day

Late afternoon

End of the day

Where to apply Diclofenac Sodium Topical Gel, 1%

Diclofenac Sodium Topical Gel, 1% can be used on up to 2 body areas from the following list: a hand, a wrist, an elbow, a foot, an ankle, a knee. Do not use on more than 2 body areas at once.

Some examples include:

Measuring the correct amount using the dosing card

For each upper body area (a hand, a wrist, or an elbow): Squeeze gel from the tube equal to the length shown on the upper body section of the dosing card (2.25 inches).

For each lower body area (a foot, an ankle, or a knee): Squeeze gel from the tube equal to the

length shown on the lower body section of the dosing card (4.5 inches).

Lost Your Dosing Card? Don't worry!

Call 1-800-719-9260 to get a free replacement.

Applying Diclofenac Sodium Topical Gel, 1%

Gently rub Diclofenac Sodium Topical Gel, 1% into the skin using your hand. Apply 4 times a day for best results. Do not use on more than 2 body areas at once.

Apply only to clean, dry skin that doesn't have any cuts, open wounds, infections or rashes. Do not apply in the same area as any other medicines or products that are applied to the skin.

Upper body areas

Elbow

Including sides, inner, and outer

Wrist

Including sides, top, and bottom

Hand

Including top, palm, and fingers

Lower body areas

Knee

Including sides, kneecap, and back

Ankle

Including sides, front, and back

Foot

Including sole, top of foot, and toes

After You Use Diclofenac Sodium Topical Gel, 1%

Wash your hands after applying Diclofenac Sodium Topical Gel, 1%. If the treated area is the hands wait up to 1 hour to wash the hands.

Wash the dosing card with water. Store dosing card with your Diclofenac Sodium Topical Gel, 1% and keep out of reach of children.

Wait ten minutes before covering the treated areas with clothes or gloves.

Avoid:

- showering or bathing for at least 1 hour after use
- exposing the treated area to sunlight or artificial light (such as in tanning booths)
- use in same area as other products applied to the skin
- applying a bandage over the treated area
- eye, nose, or mouth contact
- if eye contact occurs, rinse thoroughly with water

Facts you need to know

Important information about Diclofenac Sodium Topical Gel, 1%

Do not use Diclofenac Sodium Topical Gel, 1%...

- if you have ever had an allergic reaction to any other pain reliever or to a fever reducer
- for strains, sprains, bruises or sports injuries. This product has not been shown to work for these types of injuries.
- right before or after heart surgery
- on more than 2 body areas at the same time
- in the eyes, nose or mouth

Ask a doctor before use if...

- you have problems or serious side effects from taking pain relievers or fever reducers
- stomach bleeding warning applies to you
- you have a history of stomach problems such as heartburn
- you have high blood pressure, heart disease, liver cirrhosis, kidney disease, asthma, or had a stroke
- you are taking a diuretic
- you are under age 18 years. It is not known if this drug works or is safe in children under age 18 years.

Ask a doctor or pharmacist before use if...

- you are under a doctor's care for any serious condition
- you are taking any other drug
- you are pregnant or breast-feeding

It is especially important not to use diclofenac at 20 weeks or later in pregnancy unless definitely directed to do so by a doctor because it may cause problems in the unborn child or complications during delivery.

Warnings to consider before use...

Allergy alert

Diclofenac may cause a severe allergic reaction, especially in people allergic to aspirin. Symptoms may include:

- hives
- blisters
- asthma (wheezing)
- facial swelling
- skin reddening
- shock
- rash

If an allergic reaction occurs, stop use and seek medical help right away.

Liver warning

This product contains diclofenac. Liver damage may occur if you apply

- more or for a longer time than directed
- when using other drugs containing diclofenac

Stomach bleeding warning

This product contains an NSAID, which may cause stomach bleeding. The chance is small but higher if you

- are age 60 or older
- have had stomach ulcers or bleeding problems
- take a blood thinning (anticoagulant) or steroid drug
- take other drugs containing prescription or nonprescription NSAIDs (aspirin, ibuprofen, naproxen, or others)
- have 3 or more alcoholic drinks every day while using this product
- apply more or for longer than directed

Heart attack and stroke warning

NSAIDs, except aspirin, increase the risk of heart attack, heart failure, and stroke. This can be fatal. The risk is higher if you use more than directed or for longer than directed.

Follow these important guidelines when using Diclofenac Sodium Topical Gel, 1%...

- use only as directed
- apply only to clean, dry skin that does not have any cuts, open wounds, infections or rashes
- do not apply in the same area as any other product used on the skin
- do not apply with external heat such as heating pad
- do not apply a bandage over the treated area
- do not get gel in eyes, nose or mouth
- store ENCLOSED DOSING CARD with your Diclofenac Sodium Topical Gel, 1%. The dosing card is re-usable.

Keep out of reach of children.

If swallowed, get medical help or contact a Poison Control Center right away (1-800-222-1222).

Stop using Diclofenac Sodium Topical Gel, 1% and ask a doctor if...

- pain gets worse or lasts more than 21 days
- redness or swelling is present in the painful area
- fever occurs
- skin irritation occurs
- any new symptoms appear. These could be signs of a serious condition.
- you experience any of the following signs of stomach bleeding:
  - feel faint
  - have bloody or black stools
  - vomit blood
  - have stomach pain that does not get better
- you have symptoms of heart problems or stroke:
  - chest pain
  - trouble breathing
  - leg swelling
  - weakness in one part or side of body
  - slurred speech

Questions and Answers

Answers to questions you may ask about Diclofenac Sodium Topical Gel, 1%

Can I use Diclofenac Sodium Topical Gel, 1% for the immediate relief of pain like that associated with sprains, strains, bruises, or sports injuries?

No.

Do not use for strains, sprains, bruises, or sports injuries. This product has not been shown to work for these types of injuries. It's intended only for the temporary relief of arthritis pain.

How quickly will Diclofenac Sodium Topical Gel, 1% work for arthritis pain?

Diclofenac Sodium Topical Gel, 1% may take up to 7 days to work for your arthritis pain; it is not for immediate relief. With 4 times-a-day use, you may start to feel relief within a few days. You should feel significant pain relief within 7 days of continuous use. If no pain relief in 7 days, stop use.

What is Diclofenac Sodium Topical Gel, 1% used for?

Diclofenac Sodium Topical Gel, 1% can be used for the temporary relief of arthritis pain in the hands, wrists, elbows, feet, ankles, and knees. Osteoarthritis (OA) is the most common form of arthritis. It mainly affects a type of tissue called cartilage, which cushions the joints and prevents the bones from rubbing against each other.

With OA, cartilage begins to break down and wear away, resulting in joint pain and stiffness. OA occurs more frequently as you get older. Pain develops slowly and can gradually worsen over time.

How does Diclofenac Sodium Topical Gel, 1% work?

Diclofenac sodium, the medicine in Diclofenac Sodium Topical Gel, 1%, is a nonsteroidal anti-inflammatory drug (NSAID). NSAIDs are used to treat pain from medical conditions such as arthritis. Diclofenac Sodium Topical Gel, 1% works similarly to oral NSAIDs like ibuprofen or naproxen by temporarily blocking the production of pain signaling chemicals called prostaglandins.

However, when taking a pill, the medication is distributed to the site of pain through the bloodstream. Compared to oral diclofenac, only 6% of the medicine in Diclofenac Sodium Topical Gel, 1% is absorbed in the bloodstream. It works by penetrating through your skin at the application site to deliver arthritis pain relief.

How does over-the-counter Diclofenac Sodium Topical Gel, 1% differ from prescription Diclofenac Sodium Topical Gel, 1%?

Over-the-counter Diclofenac Sodium Topical Gel, 1% is the same strength and formula as original full prescription strength Diclofenac Sodium Topical Gel, 1% but is available without a prescription.

Apply Diclofenac Sodium Topical Gel, 1% 4 times a day to ensure you get the full effect of the medicine.

Can I apply Diclofenac Sodium Topical Gel, 1% to upper and lower body areas at the same time?

Yes.

You can use Diclofenac Sodium Topical Gel, 1% on up to 2 body areas at the same time. The areas can include the foot, ankle, knee, hand, wrist, and elbow.

Some correct examples include:

Upper body

Hand and elbow

Lower body

Knee and ankle

Upper/Lower body

Wrist and ankle

Lower body

(L)Knee and (R)knee

Do not use Diclofenac Sodium Topical Gel, 1% on more than 2 body areas at once.

Can I apply Diclofenac Sodium Topical Gel, 1% without measuring it out on the dosing card first?

No.

Use the dosing card to make sure you are getting the correct amount of medicine.

Can I use Diclofenac Sodium Topical Gel, 1% on my spine, hips, or shoulders?

No.

The use of Diclofenac Sodium Topical Gel, 1% on the spine, hips, and shoulders has not been studied.

Can I take any other pain medications with Diclofenac Sodium Topical Gel, 1%?

Ask your doctor or pharmacist before using Diclofenac Sodium Topical Gel, 1% if you are taking any other pain reliever or are planning on taking any other pain reliever, especially prescription or nonprescription NSAIDs (aspirin, ibuprofen, naproxen, or others).

Can I take any other pain medications during the first 7 days I use Diclofenac Sodium Topical Gel, 1%?

Taking other pain medications is generally not recommended. Speak with your doctor or pharmacist before taking other pain medications when using Diclofenac Sodium Topical Gel, 1%.

How long can I use Diclofenac Sodium Topical Gel, 1%?

Use Diclofenac Sodium Topical Gel, 1% 4 times a day every day for up to 21 days for treatment of arthritis pain or as directed by your doctor.

Diclofenac Sodium Topical Gel, 1% should be part of an overall program for managing your arthritis pain. The program should also include activities such as appropriate movement or exercise, specific lifestyle changes, and weight maintenance. Regular visits and discussions with your doctor can help incorporate Diclofenac Sodium Topical Gel, 1% into a complete program to help manage your arthritis pain.

What do I do if I get Diclofenac Sodium Topical Gel, 1% in my eyes?

If eye contact occurs, rinse thoroughly with water and consult a doctor if irritation lasts more than an hour.

How do I clean the dosing card?

Wash the dosing card with water, and store dosing card and tube out of reach of children.

What if I miss a dose of Diclofenac Sodium Topical Gel, 1%?

If you forget to apply Diclofenac Sodium Topical Gel, 1% don't double your dose. Just apply the next dose as scheduled.

How should I store Diclofenac Sodium Topical Gel, 1%?

- Store at 20-25°C (68-77° F).
- Do not freeze Diclofenac Sodium Topical Gel, 1%.
- Store the dosing card with your Diclofenac Sodium Topical Gel, 1%.
- Keep out of reach of children.

Additional Questions?

Call 1-800-719-9260.

Distributed By

Perrigo®

Allegan, MI 49010

94V00 00 J1

Package/Label Principal Display Panel

CVS Health®

COMPARE TO the active ingredient in Voltaren® Arthritis Pain

ORIGINAL PRESCRIPTION STRENGTH

Diclofenac Sodium Topical Gel, 1% (NSAID)

ARTHRITIS PAIN RELIEVER

• For daily treatment of arthritis pain

• Anti-inflammatory

For External Use Only

Medicated gel clinically proven to relieve arthritis pain

NET WT 5.29 OZ (150 g)

Package Contains One Tube